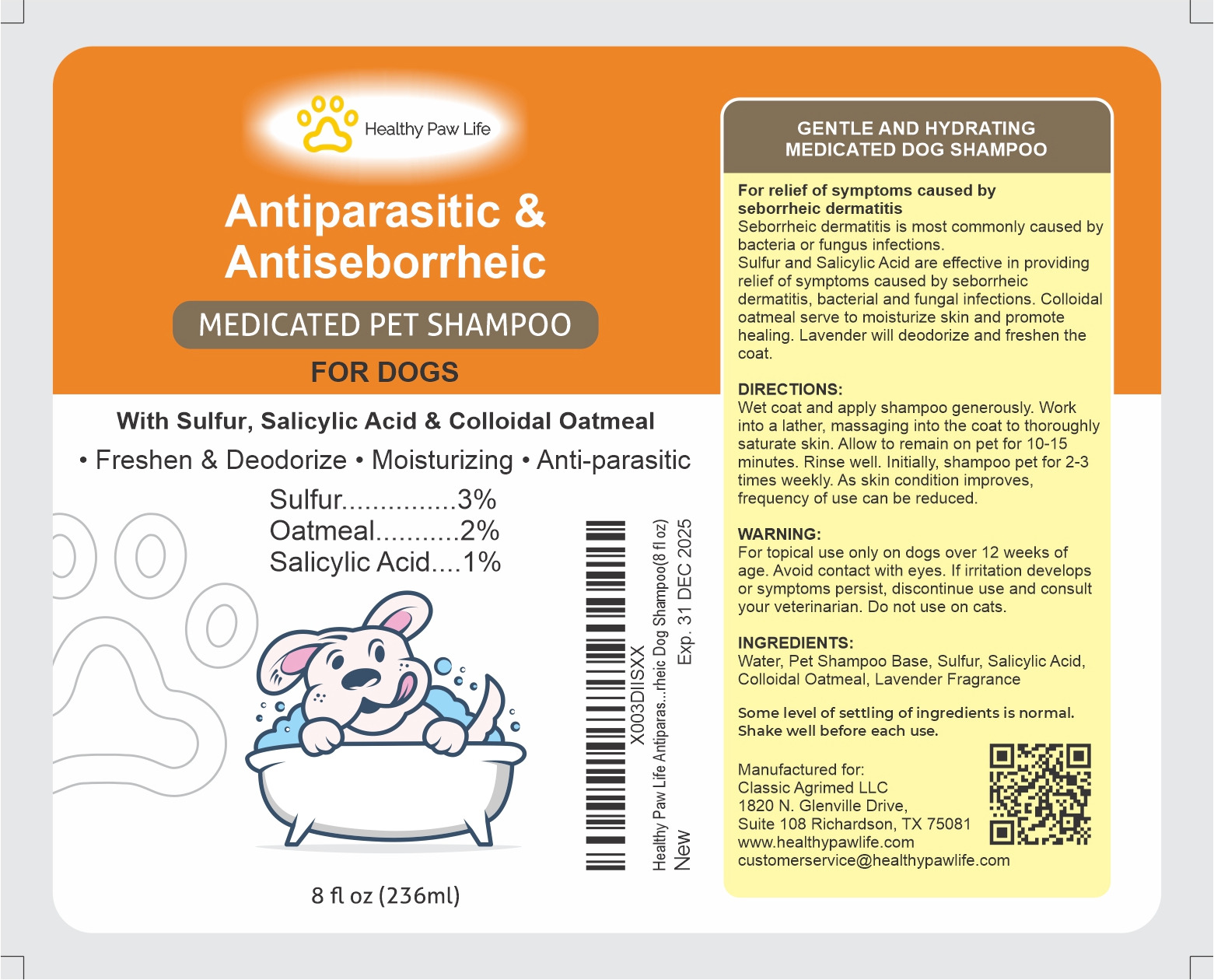 DRUG LABEL: HEALTHY PAW LIFE
NDC: 86130-800 | Form: SHAMPOO
Manufacturer: CLASSIC AGRIMED LLC
Category: animal | Type: OTC ANIMAL DRUG LABEL
Date: 20231109

ACTIVE INGREDIENTS: SULFUR 7 g/236 g; SALICYLIC ACID 2 g/236 g; OATMEAL 5 g/236 g

CLASSIC SULFUR, SALICYLIC ACID OATMEAL

Label Description

For relief of symptoms caused by seborrheic dermatitis.

Seborrheic Dermatitis is most commonly caused by bacteria or fungus infections.

Sulfur and Salicylic Acid are effective in providing releif of symptoms caused by seborrheic dermatitis, bacterial and fungal infoections.Colloidal oatmeal serve to moisture skin and promote healing. Lavender will deodorize and freshen the coat.

DIRECTIONS:

Wet coat and apply shampoo generously. Work into a thicker lather, massaging into the coat to thoroughly saturate skin. Allow to remain on pet for 10-15 minutes. Rinse well. Initially shampoo pet 2-3 times weekly. As skin condition improves, frequency of use can be reduced

WARNING:

For topical use only on dogs ove 12 weeks of age. Avoid contact with eyes. If irritation develops or symptoms persist, discontinue use and consult your veterinarian. Do not use on cats.

INGREDIENTS:

Water, Pet Shampoo Base, Sulfur, Salicylic Acid, Colloidal Oatmeal, Lavender Fragrence.

Manufactured For:

Classic Agrimed LLC